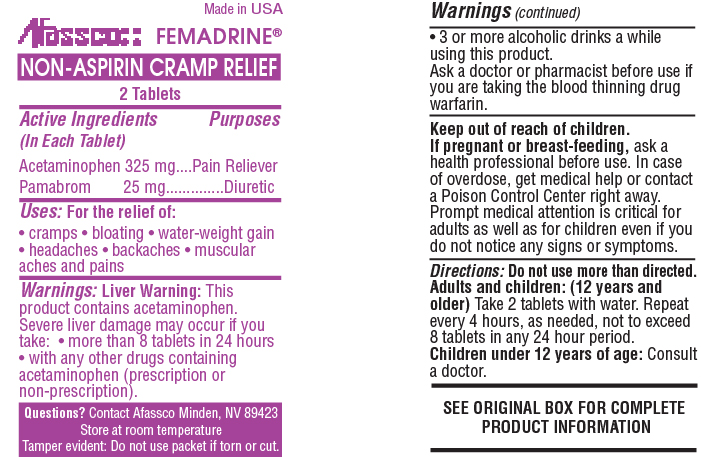 DRUG LABEL: Femadrine
NDC: 51532-0700 | Form: TABLET
Manufacturer: Afassco Inc.
Category: otc | Type: HUMAN OTC DRUG LABEL
Date: 20161128

ACTIVE INGREDIENTS: ACETAMINOPHEN 325 1/1 1; PAMABROM 25 1/1 1
INACTIVE INGREDIENTS: MICROCRYSTALLINE CELLULOSE; D&C YELLOW NO. 10; FD&C BLUE NO. 1; FD&C RED NO. 40; POVIDONE; STARCH, CORN; STEARIC ACID; RAW SUGAR

Drug Facts

ACTIVE INGREDIENT

Acetaminophen 325mg

Pamabrom 25mg

PURPOSE

Pain reliever, Diuretic

INDICATIONS AND USAGE

Uses: For the relief of:

• cramps • bloating • water-weight gain

• headaches • backaches • muscular aches and pains

Warnings:

Liver Warning: This product contains acetaminophen. Severe liver damage may occur if you take: • more than 8 tablets in 24 hours

• with any other drugs containing acetaminophen (prescription or non-prescription).

• 3 or more alcoholic drinks a while using this product.

Ask a doctor or pharmacist before use if you are taking the blood thinning drug warfarin.

Keep out of reach of children.

PREGNANCY OR BREAST FEEDING

If pregnant or breast-feeding, ask a health professional before use.

OVERDOSAGE

In case of overdose, get medical help or contact a Poison Control Center right away. Prompt medical attention is critical for adults as well as for children even if you do not notice any signs or symptoms.

DOSAGE AND ADMINISTRATION

Directions: Do not use more than directed.

Adults and children: (12 years and older) Take 2 tablets with water. Repeat every 4 hours, as needed, not to exceed 8 tablets in any 24 hour period.

Children under 12 years of age: Consult a doctor.

INACTIVE INGREDIENT

SEE ORIGINAL BOX FOR COMPLETE PRODUCT INFORMATION